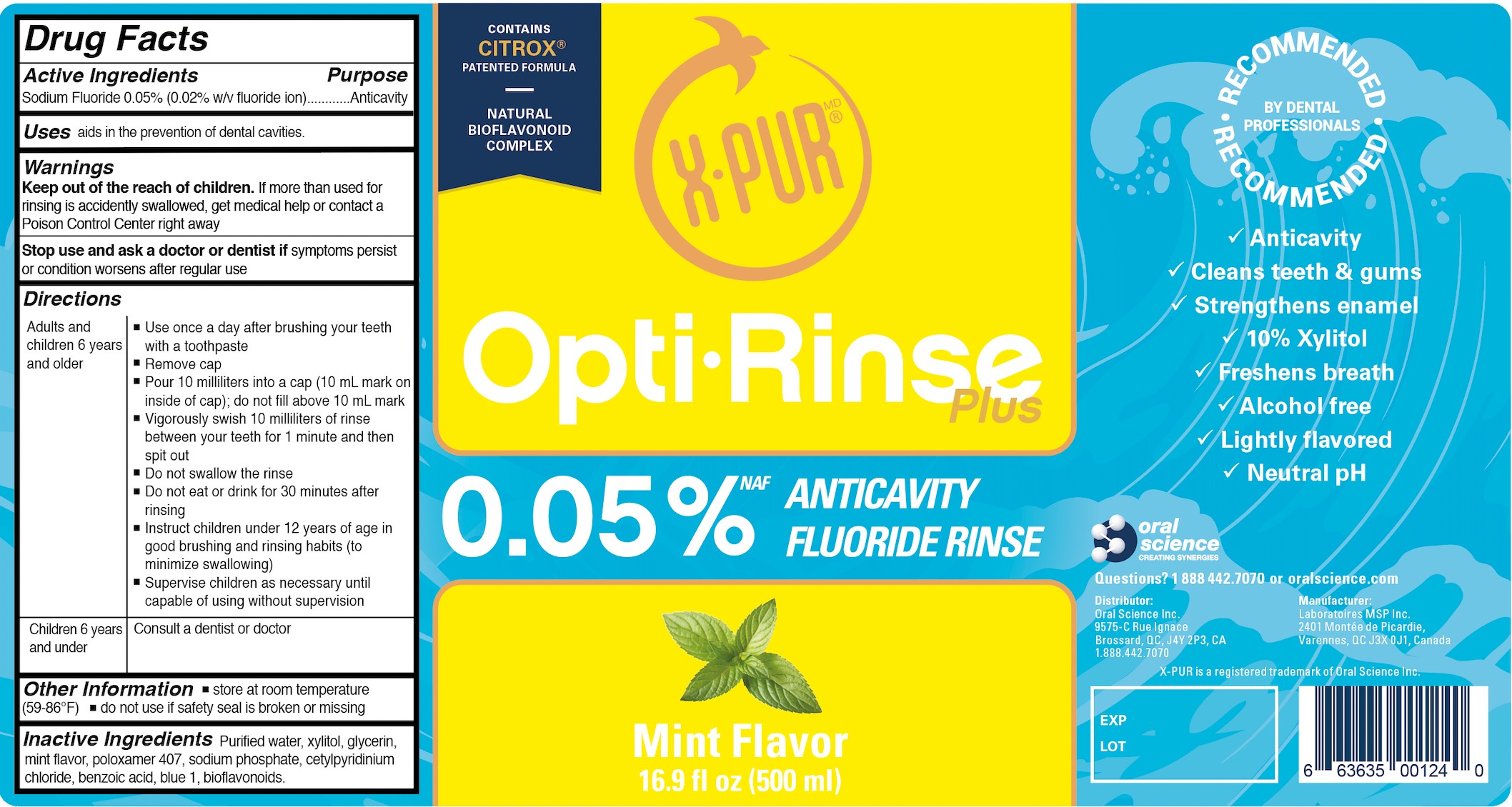 DRUG LABEL: X-Pur Opti-Rinse Plus
NDC: 81359-114 | Form: MOUTHWASH
Manufacturer: Oral Science Inc
Category: otc | Type: HUMAN OTC DRUG LABEL
Date: 20221029

ACTIVE INGREDIENTS: SODIUM FLUORIDE 0.05 g/100 mL
INACTIVE INGREDIENTS: FD&C BLUE NO. 1; BENZOIC ACID; XYLITOL; POLOXAMER 407; CETYLPYRIDINIUM CHLORIDE; MINT; GLYCERIN; CITRUS BIOFLAVONOIDS; WATER; SODIUM PHOSPHATE

Oral Science-Laboratoires MSP- X-Pur Mint Mouthwash

Active Ingredient(s)

Sodium Fluoride 0.05% (0.02% w/v fluoride ion)............Anticavity

Purpose

Anticavity

Use

aids in the prevention of dental cavities.

Warnings

Keep out of the reach of children. If more than used for rinsing is accidentally swallowed, get medical help or contact a Poison Control Center right away

Stop use and ask a doctor or dentist if symptoms persist or condition worsens after regular use

Stop use and ask a doctor or dentist if symptoms persist or condition worsens after regular use

KEEP OUT OF REACH OF CHILDREN

If more than used for rinsing is accidently swallowed, get medical help or contact a Poison Control Center right away

Directions

- Adults and children 6 years and older:

Use once a day after brushing your teeth with a toothpaste
Remove cap
Pour 10 milliliters into a cap (10 mL mark on the inside of cap); do not fill above 10 mL mark Vigorously swish 10 milliliters of rinse between your teeth for 1 minute and then spit out

Do not swallow the rinse
Do not eat or drink for 30 minutes after rinsing
Instruct children under 12 years of age in good brushing and rinsing habits (to minimize swallowing)
Supervise children as necessary until capable of using without supervision

- Children 6 years and under

Consult a dentist or doctor

Inactive ingredients

water, xylitol, glycerin, poloxamer 407, sodium phosphate, bioflavonoids, benzoic acid, cetylpyridinium chloride, mint flavor, blue 1

OTHER SAFETY INFORMATION

store at room temperature (59-86°F) do not use if safety seal is broken or missing

Package Label - Principal Display Panel

500 mL NDC: 81359-114-11